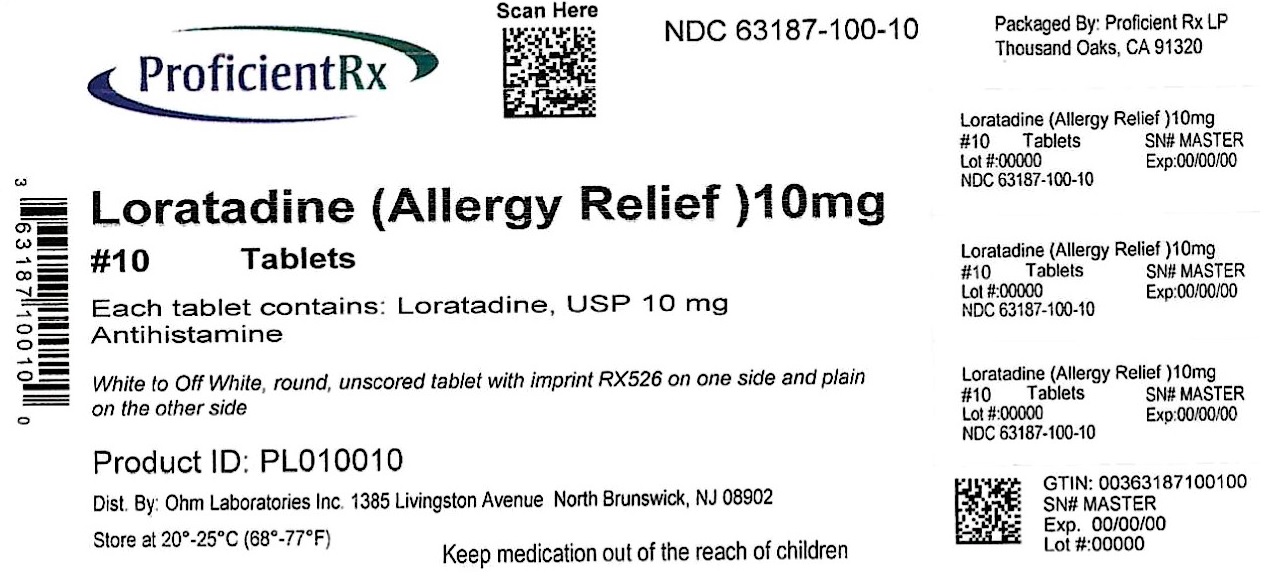 DRUG LABEL: Loratadine Allergy Relief
NDC: 63187-100 | Form: TABLET
Manufacturer: Proficient Rx LP
Category: otc | Type: HUMAN OTC DRUG LABEL
Date: 20241001

ACTIVE INGREDIENTS: LORATADINE 10 mg/1 1
INACTIVE INGREDIENTS: STARCH, CORN; LACTOSE MONOHYDRATE; MAGNESIUM STEARATE

Drug Facts

ACTIVE INGREDIENT(S)

Loratadine USP, 10 mg

PURPOSE

Antihistamine

USE(S)

Temporarily relieves these symptoms due to hay fever or other upper respiratory allergies:

- runny nose
- itchy, watery eyes
- sneezing
- itching of the nose or throat

WARNINGS

Do not use

If you have ever had an allergic reaction to this product or any of its ingredients.

Ask a doctor before use if you have

Liver or kidney disease. Your doctor should determine if you need a different dose.

When using this product

Do not take more than directed. Taking more than directed may cause drowsiness.

Stop use and ask a doctor if

An allergic reaction to this product occurs. Seek medical help right away.

If pregnant or breast-feeding,

Ask a health professional before use.

Keep out of reach of children.

In case of overdose, get medical help or contact a Poison Control Center right away.

DIRECTIONS

adults and children 6 years and over | 1 tablet daily; not more than 1 tablet in 24 hours
children under 6 years of age | ask a doctor
consumers with liver and kidney disease | ask a doctor

OTHER INFORMATION

- store between 20 and 25° C (68 and 77° F)
- protect from excessive moisture
- TAMPER EVIDENT: DO NOT USE IF IMPRINTED SEAL IS BROKEN OR MISSING FROM BOTTLE.

INACTIVE INGREDIENTS

Corn starch, lactose monohydrate, magnesium stearate, pregelatinized starch

QUESTIONS?

Call 1-800-406-7984

PRINCIPAL DISPLAY PANEL

NDC 63187-100-10

† Compare to the active ingredient of Claritin®

NON-DROWSY*

24 HourAllergy Relief

Loratadine Tablets USP, 10 mg

Antihistamine

Indoor & Outdoor Allergies

Relief of:

- Sneezing
- Runny Nose
- Itchy, Watery Eyes
- Itchy Throat or Nose

10 Tablets

When taken as directed. See Drug Facts Panel.

Manufactured by: Ohm Laboratories Inc.

5069178/0908

Repackaged by:

Proficient Rx LP

Thousand Oaks, CA 91320